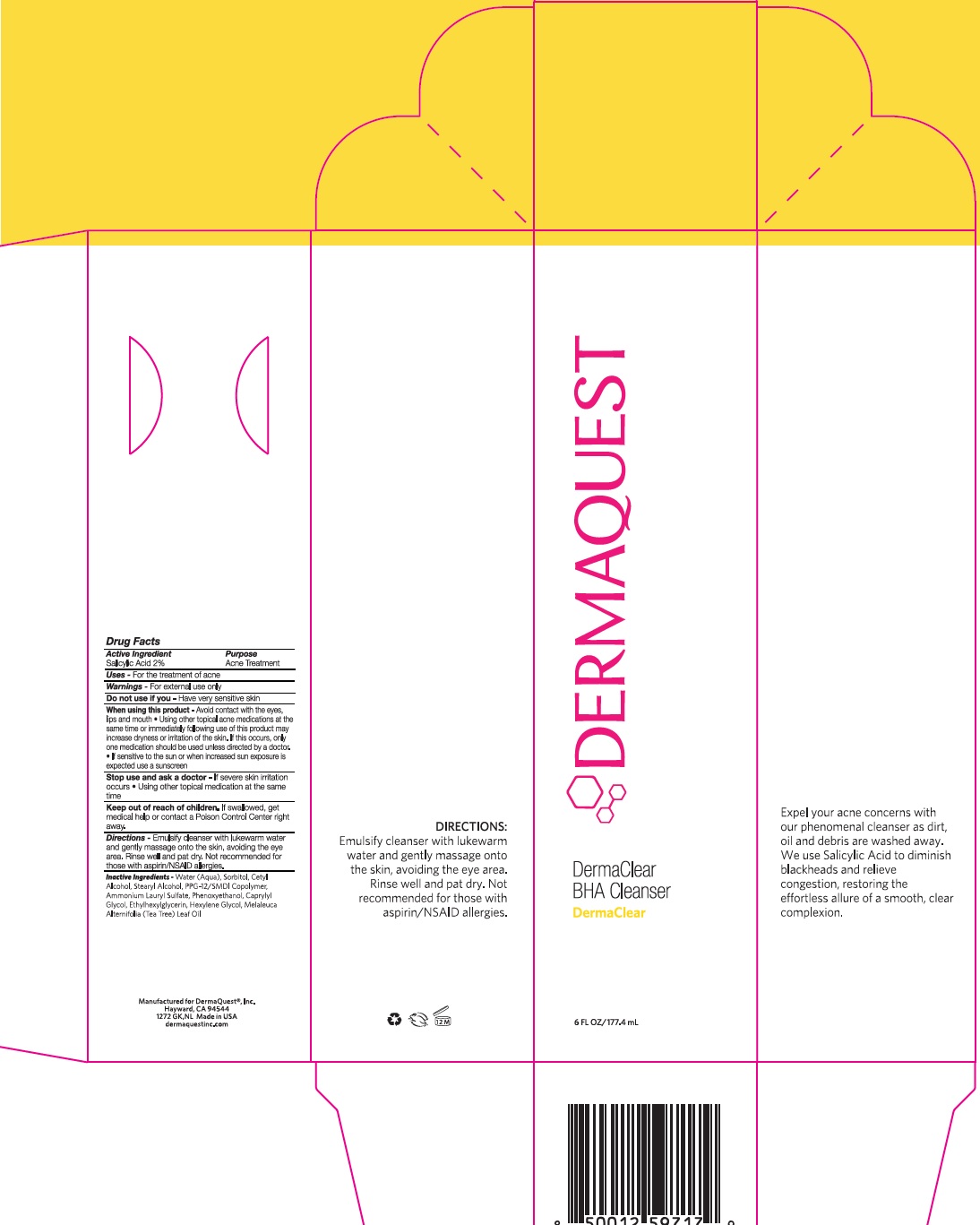 DRUG LABEL: DermaClear BHA Cleanser
NDC: 62742-4065 | Form: LOTION
Manufacturer: Allure Labs Inc
Category: otc | Type: HUMAN OTC DRUG LABEL
Date: 20241203

ACTIVE INGREDIENTS: SALICYLIC ACID 2 mg/1 mL
INACTIVE INGREDIENTS: CETYL ALCOHOL; TEA TREE OIL; STEARYL ALCOHOL; AMMONIUM LAURYL SULFATE; WATER; SORBITOL; PPG-12/SMDI COPOLYMER; PHENOXYETHANOL; CAPRYLYL GLYCOL; ETHYLHEXYLGLYCERIN; HEXYLENE GLYCOL

Drug Facts

Active Ingredient: Salicylic Acid 2%

Purpose: Acne Treatment

INDICATIONS AND USAGE

Uses - Fot the treatment of acne

Do not use if you - have very sensitive skin

When using this product -

- Avoid contact with the eyes, lips and mouth
- Using other topical acne medication at the same time or immediately following use of this product may increase dryness or irritation of the skin. If this occurs, only one medication should be used unless directed by a doctor.
- If sensitive to the sun or when increased sun exposure is expected use a sunscreen

Stop use and ask a doctor -

- if severe skin irritation occurs
- Using other topical medication at the same time

Keep out of reach of children. If swallowed , get medical help or contact a Poison Cotrol Center right away.

DOSAGE AND ADMINISTRATION

Directions - Emulsify cleanser with lukewarm water and gently massage onto the skin, avoiding the eye area. Rinse well and pat dry. Not recommended for those with asprin / NASID allergies.

Inactive Ingredients -

Water (Aqua), Sorbitol, Cetyl Alcohol, Stearyl Alcohol, PPG12/'SMDI Copolymer, Ammonium Lauryl Sulfate, Phenoxyethanol, Caprylyl Glycol, Ethylhexylglycerin, Hexylene Glycol, Melaleuca (Tea Tree) Alternifolia Leaf Oil

Warnings - For external use only

PACKAGE LABEL

Manufactured for Dermaquest®, Inc.

Hayward, CA - 94544

1272 GK,NL Made in USA

Dermaquest Inc.